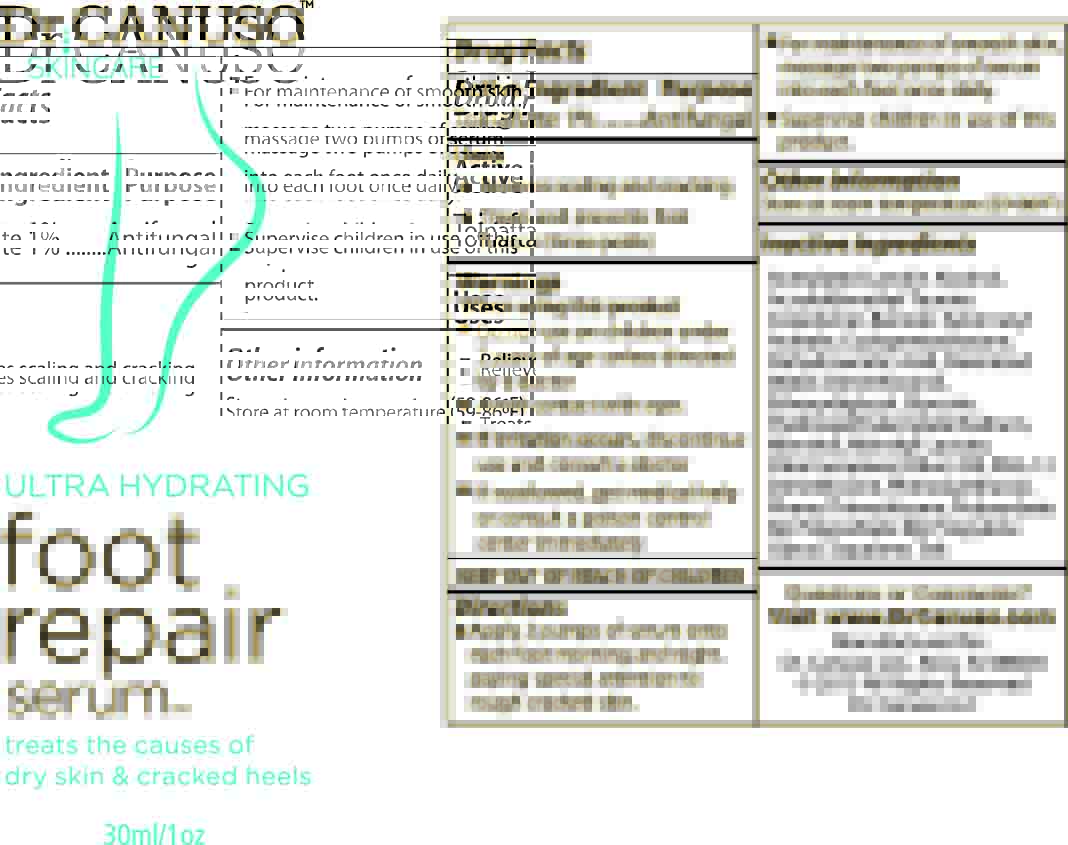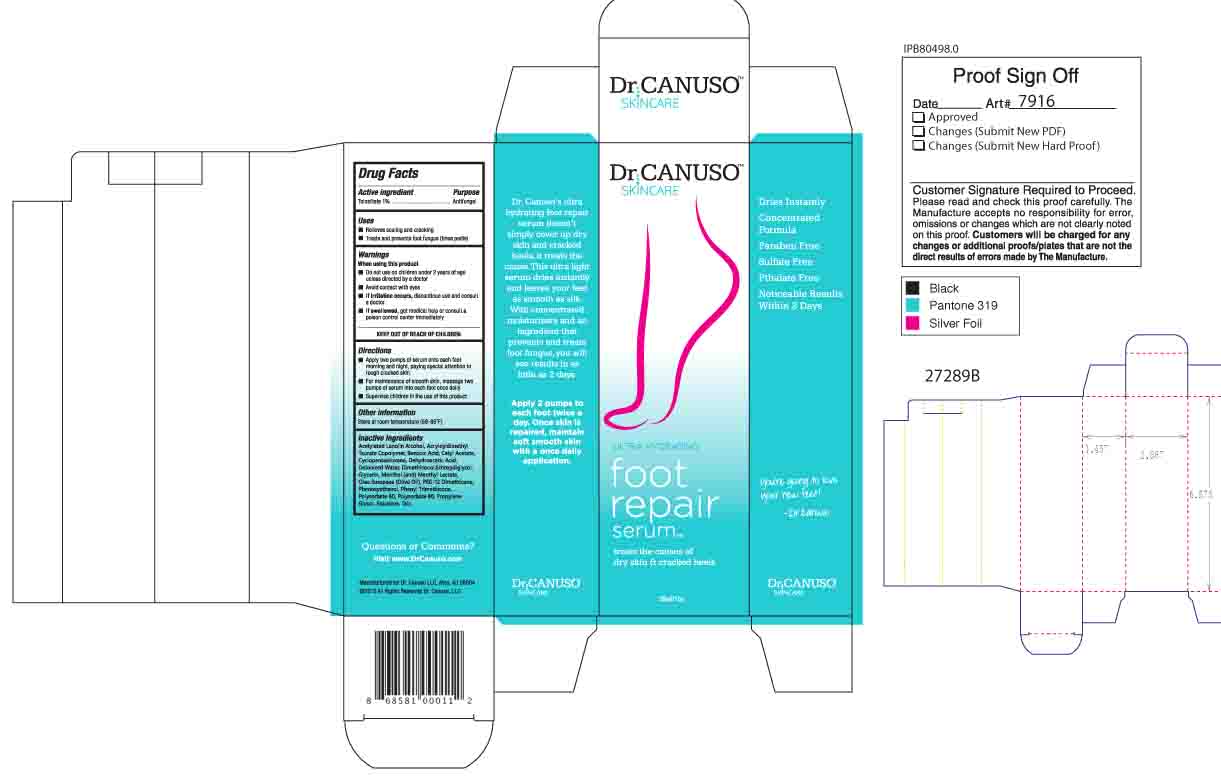 DRUG LABEL: Dr. Canuso foot repair serum
NDC: 76348-409 | Form: LOTION
Manufacturer: Renu Laboratories, LLC
Category: otc | Type: HUMAN OTC DRUG LABEL
Date: 20250513

ACTIVE INGREDIENTS: TOLNAFTATE 0.3 g/28 g
INACTIVE INGREDIENTS: DEHYDROACETIC ACID; TALC; POLYSORBATE 80; PROPYLENE GLYCOL; PEG-12 DIMETHICONE (300 CST); GLYCERIN; CETYL ACETATE; ACETYLATED LANOLIN ALCOHOLS; WATER; MENTHYL LACTATE, (-)-; DIMETHICONE; CYCLOMETHICONE 5; PHENYL TRIMETHICONE; 2-HYDROXYETHYL ACRYLATE; SODIUM ACRYLOYLDIMETHYLTAURATE; SQUALANE; POLYSORBATE 60; PHENOXYETHANOL; BENZOIC ACID; OLIVE OIL; DIETHYLENE GLYCOL MONOETHYL ETHER; MENTHOL

Dr. Canuso foot repair serum TM

ACTIVE INGREDIENT

Tolnaftate 1%

PURPOSE

Antifungal

When using this product

- Do not use on children under 2 years of age unless directed by a doctor
- Avoid contact with eyes
- If irritation occurs, discontinue use and consult a doctor
- If swallowed, get medical help or consult a poison control center immediately

KEEP OUT OF REACH OF CHILDREN

Other Information

Store at room temperature (59-86º F)

Inactive Ingredients

Acetylated Lanolin Alcohol, Acryloyldimethyl Taurate Copolymer, Benzoic Acid, Cetyl Acetate, Cyclopentasiloxane, Dehydroacetic Acid, Deionized Water, Dimethiconol, Ethoxydiglycol, Glycerin, Menthol, Menthyl Lactate, Olea Europaea (Olive Oil), PEG-12 Dimethicone, Phenoxyethanol, Phenyl Trimethicone, Polysorbate 60, Polysorbate 80, Propylene Glycol, Squalane, Talc.

Questions or Comments?
Visit www.DrCanuso.com

Directions

- Apply two pumps of serum onto each foot morning and night, paying special attention to rough cracked skin.
- For maintenance of smooth skin, massage two pumps of serum into each foot once daily.
- Supervise children in the use of this product.

Directions

- Apply two pumps of serum onto each fot morning and night, paying special attention to rough cracked skin.